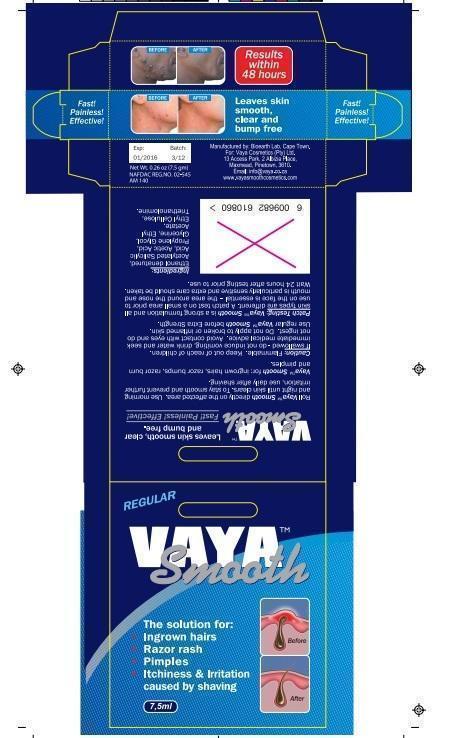 DRUG LABEL: Vaya Smooth Female
NDC: 62955
Manufacturer: Vaya Smooth Cosmetics (Pty) Ltd
Category: other | Type: COSMETIC
Date: 20151019

Vaya Smooth Aftershave

PACKAGE LABEL.PRINCIPAL DISPLAY PANEL Vaya Smooth packaging label male-7.5.jpg

Vaya Smooth packaging label Female7.5.jpg